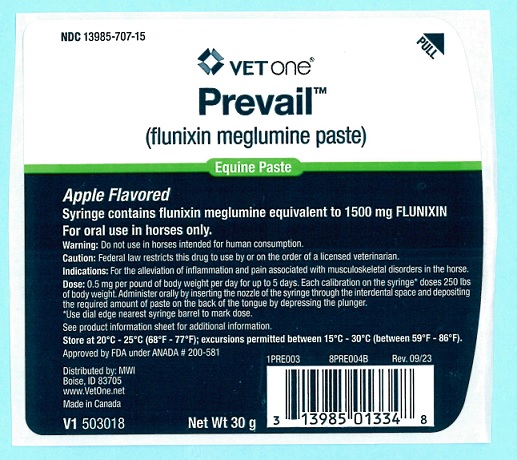 DRUG LABEL: Prevail
NDC: 13985-707 | Form: PASTE
Manufacturer: MWI
Category: animal | Type: PRESCRIPTION ANIMAL DRUG LABEL
Date: 20240401

ACTIVE INGREDIENTS: FLUNIXIN MEGLUMINE 1500 mg/30 g

DESCRIPTION

Prevail®
(flunixin meglumine paste)
Equine Paste

Apple Flavored

CAUTION: Federal law restricts this drug to use by or on the order of a licensed veterinarian.

DESCRIPTION: Each 30-g syringe of Flunazine Equine Paste contains flunixin meglumine equivalent to 1500 mg flunixin.

INDICATIONS AND USAGE

INDICATIONS: Prevail Equine Paste is recommended for the alleviation of inflammation and pain associated with musculoskeletal disorders in the horse.

ACTIVITY: Flunixin meglumine is a potent, nonnarcotic, nonsteroidal, analgesic agent with anti-inflammatory and antipyretic activity. It is significantly more potent than pentazocine, meperidine, and codeine as an analgesic in the rat yeast paw test. Oral studies in the horse show 1 onset of flunixin activity occurs within 2 hours of administration. Peak response occurs between 12 and 16 hours and duration of activity is 24 to 36 hours.

WARNINGS AND PRECAUTIONS

For oral use in horses only

CONTRAINDICATIONS: There are no known contraindications to this drug when used as directed.
WARNING: Do not use in horses intended for human consumption.

PRECAUTIONS: The effect of flunixin meglumine on pregnancy has not been determined. Studies to date show there is no detrimental effect on stallion spermatogenesis with or following the recommended dose of flunixin meglumine.
SIDE EFFECTS: During field studies with flunixin meglumine, no significant side effects were reported.

To report suspected adverse drug events, for technical assistance or to obtain a copy of the Safety Data Sheet (SDS), contact Bimeda, Inc. at 1-888-524-6332. For additional information about adverse drug experience reporting for animal drugs, contact FDA at 1-888-FDA-VET or online at www.fda.gov/reportanimalaeduration of activity is 24 to 36 hours.

DOSAGE AND ADMINISTRATION: The recommended dose of flunixin is 0.5 mg per lb of body weight once daily. The Prevail Equine Paste syringe, calibrated in twelve 250-lb weight increments, delivers 125 mg of flunixin for each 250 lbs (see dosage table). One syringe will treat a 1000-lb horse once daily for 3 days, or three 1000-lb horses one time.

DOSAGE TABLE

Syringe Mark* | Horse Weight (lbs) | Prevail™ Equine Paste Delevered (g) | mg flunixin Delivered
0 | --- | --- | ---
250 | 250 | 2.5 | 125
500 | 500 | 5.0 | 250
750 | 750 | 7.5 | 375
1000 | 1000 | 10.0 | 500

* Use dial edge nearest syringe barrel to mark dose.

The paste is orally administered by inserting the nozzle of the syringe through the interdental space, and depositing the required amount of paste on the back of the tongue by depressing the plunger.

Treatment may be given initially by intravenous or intramuscular of Prevail™ Injectable Solution, followed by Prevail™ Equine Paste on Days 2 to 5. Flunixin meglumine treatment should not exceed 5 consecutive days.

TOXICITY: No toxic effects were observed in rats given oral flunixin meglumine 2 mg/kg per day for 42 days. Higher doses produced ulceration of the gastrointestinal tract. The emetic dose in dogs is between 150 and 250 mg/kg. Flunixin was well tolerated in monkeys dosed daily with 4 mg/kg for 56 days. No adverse effects occurred in horses dosed orally with 1.0 or 1.5 mg/lb for 5 consecutive days.

STORAGE AND HANDLING

Store at 20°C - 25°C (68°F - 77°F); excursions permitted between 15°C - 30°C (between 59°F - 86°F)

See product information sheet for additional information.

Approved by FDA under ANADA # 200-581